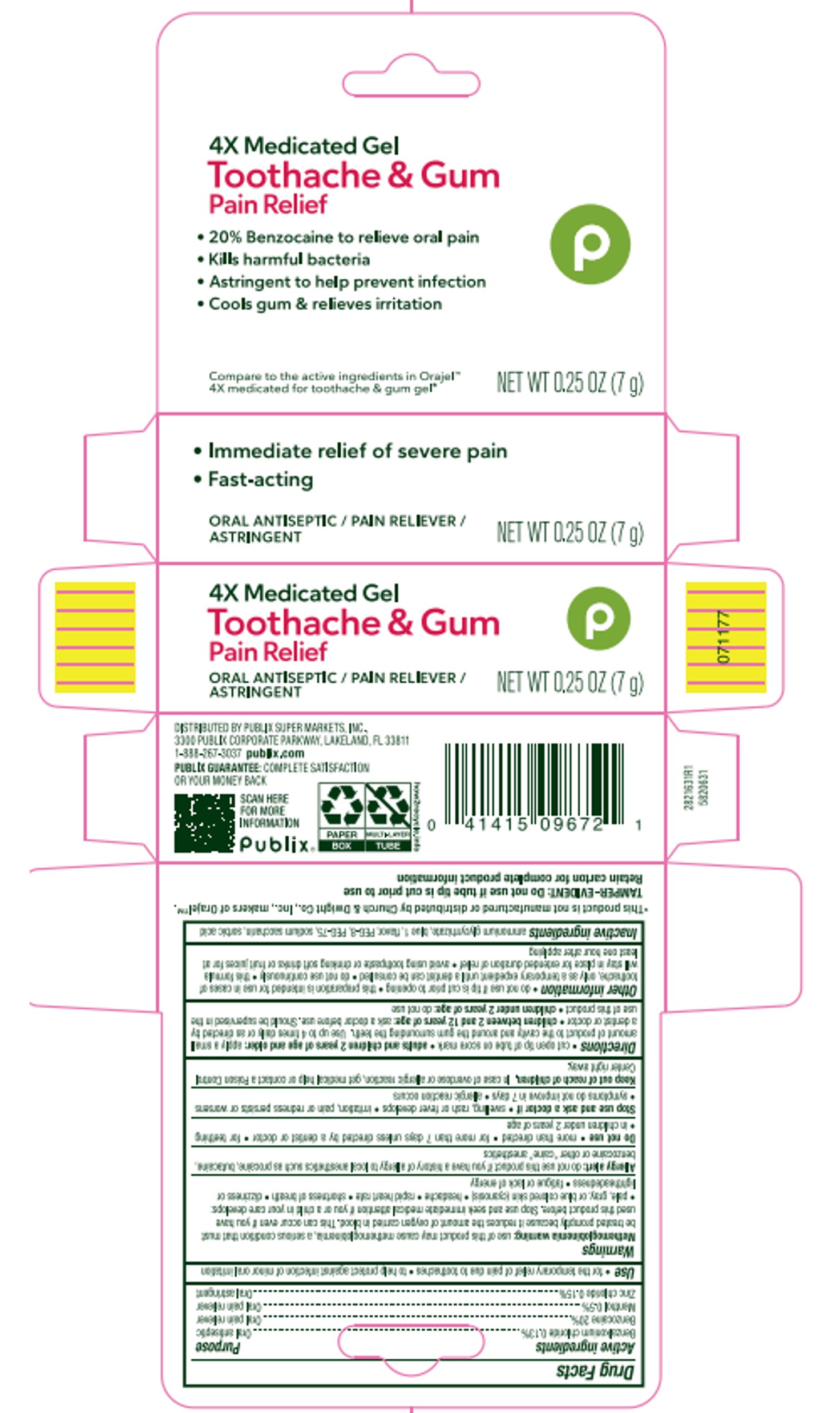 DRUG LABEL: 4x Medicated Toothache and Gum Gel
NDC: 56062-312 | Form: GEL, DENTIFRICE
Manufacturer: Publix Super Markets INC
Category: otc | Type: HUMAN OTC DRUG LABEL
Date: 20250812

ACTIVE INGREDIENTS: BENZOCAINE 20 g/100 g; BENZALKONIUM CHLORIDE 0.13 g/100 g; ZINC CHLORIDE 0.15 g/100 g; MENTHOL 0.5 g/100 g
INACTIVE INGREDIENTS: POLYETHYLENE GLYCOL 3350; FD&C BLUE NO. 1; SORBIC ACID; POLYETHYLENE GLYCOL 400; METHYL SALICYLATE; SACCHARIN SODIUM; AMMONIUM GLYCYRRHIZATE

5820631 Publix 4x Medicated Toothache & Gum Gel (8015602)

Drug Facts

ACTIVE INGREDIENT

Benzalkonium chloride 0.13%

Benzocaine 20%

Menthol 0.5%

Zinc Chloride 0.15%

PURPOSE

Oral antiseptic

Oral pain reliever

Oral astringent

INDICATIONS AND USAGE

temporary relief of pain due to toothache * to help protect against infection of minor oral irritation

WARNINGS

Methemoglobinemia warning: use of this product may cause methemoglobinemia, a serious condition that must be treated promptly because it reduces the amount of oxygen carried in blood. This can occur even if you have used this product before. Stop use and seek immediate medical attention if you or a child in your care develops:

pale, gray, or blue colored skin (cyanosis)

headache

rapid heart rate

shortness of breath

dizziness or lightheadness

fatique or lack of energy

Alergy alert: do not use this product if you have a history of allergy to local anesthetics such as procaine, butacaine, benzocaine or other "caine" anesthetics

Do not use:

more than directed

for more than 7 days unless directed by a dentist or doctor

for teething

in children under 2 years of age

Stop use and ask a doctor if

swelling, rash or fever develops

irritation, pain or redness persists or worsens

symptoms do not improve in 7 days

allergic reaction occurs

Keep out of reach of children. In case of overdose or allergic reaction, get medical help or contact a Poison Control Center right away.

Directions

cut open tip of tube on score mark

adults and children 2 years of age and older: apply a small amount of product to the cavity and around the gum surrounding the teeth. Use up to 4 times daily or as directed by a dentist or doctor.

children between 2 and 12 years of age: ask a doctor before use. Should be supervised in the use of this product

children under 2 years of age: do not use

do not use if tip is cut prior to opening * this preparation is intended for use in cases of toothache, only as a temporary expedient until a dentist can be consulted *do not use continuously *this formula will stay in place for extended duration of relief *avoid using toothpaste or drinking soft drinks or fruit juices for at least one hour after applying

INACTIVE INGREDIENT

ammonium glycyrrhizate, blue 1, flavor, PEG-8, PEG-75, sodium saccharin, sorbic acid

DISTRIBUTED BY:

PUBLIX SUPER MARKETS, 3300 PUBLIX CORPORATE PARKWAY

LAKELAND, FL 33811

PACKAGE LABEL

PUBLIX SUPER MARKETS, INC

4X MEDICATED GEL

TOOTHACHE & GUM PAIN RELIEF

- 20% Benzocaine to relieve oral pain
- Kills harmful bacteria
- Astringent to help prevent infection
- Cools gum & relieves irritation

Compare to the active ingredients in Orajel

4X medicated for toothache & Gum gel*

NET WT 0.25OZ (7 g)